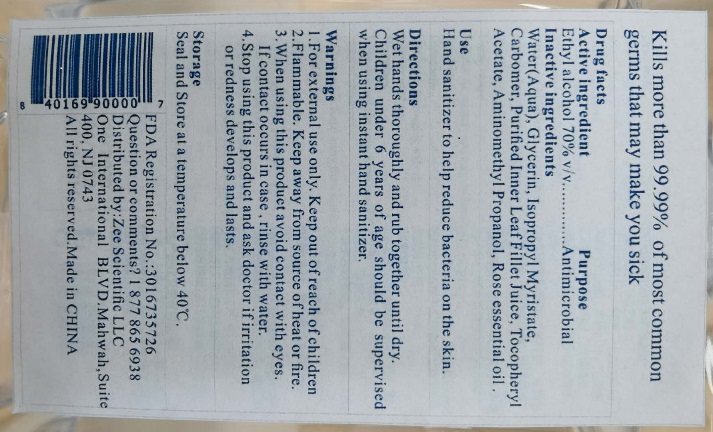 DRUG LABEL: Instant hand sanitizer
NDC: 78766-001 | Form: GEL
Manufacturer: Zhejiang Bayside Biotech Co., Ltd.
Category: otc | Type: HUMAN OTC DRUG LABEL
Date: 20200619

ACTIVE INGREDIENTS: ALCOHOL 70 1/100 mL
INACTIVE INGREDIENTS: GLYCERIN 3 1/100 mL; ISOPROPYL MYRISTATE 0.5 1/100 mL; WATER 25.9 1/100 mL; AMINOMETHYLPROPANOL 0.04 1/100 mL; ALPHA-TOCOPHEROL ACETATE 0.05 1/100 mL; ALOE FEROX LEAF 0.1 1/100 mL; CARBOMER 940 0.4 1/100 mL; ROSE OIL 0.01 1/100 mL

Active Ingredient(s)

Alcohol 70% v/v. Purpose: Antimicrobial

Purpose

Antimicrobial, Hand Sanitizer

Use

Hand Sanitizer to help reduce bacteria on the skin.

Warnings

- For external use only. Keep out of reach of children.
- Flammable. Keep away from source of heat or fire.

Do not use

- in children less than 2 months of age
- on open skin wounds

When using this product avoid contact with eyes. If contact occurs in case, rinse with water.

STOP USE

Stop using this product and ask doctor if irritation or redness develops and lasts.

Keep out of reach of children.

Directions

- Wet hands thoroughly and rub together until dry.
- Children under 6 years of age should be supervised when using instant hand sanitizer.

Other information

- Seal and store at a temperature below 40C (104F)

Inactive ingredients

glycerin, water, Isopropyl Myristate, Carbomer, Aloe Leaf juice, Tocopheryl Acetate, Aminomethyl propanol, Rose oil.

Package Label - Principal Display Panel

266 mL NDC: 78766-001-01